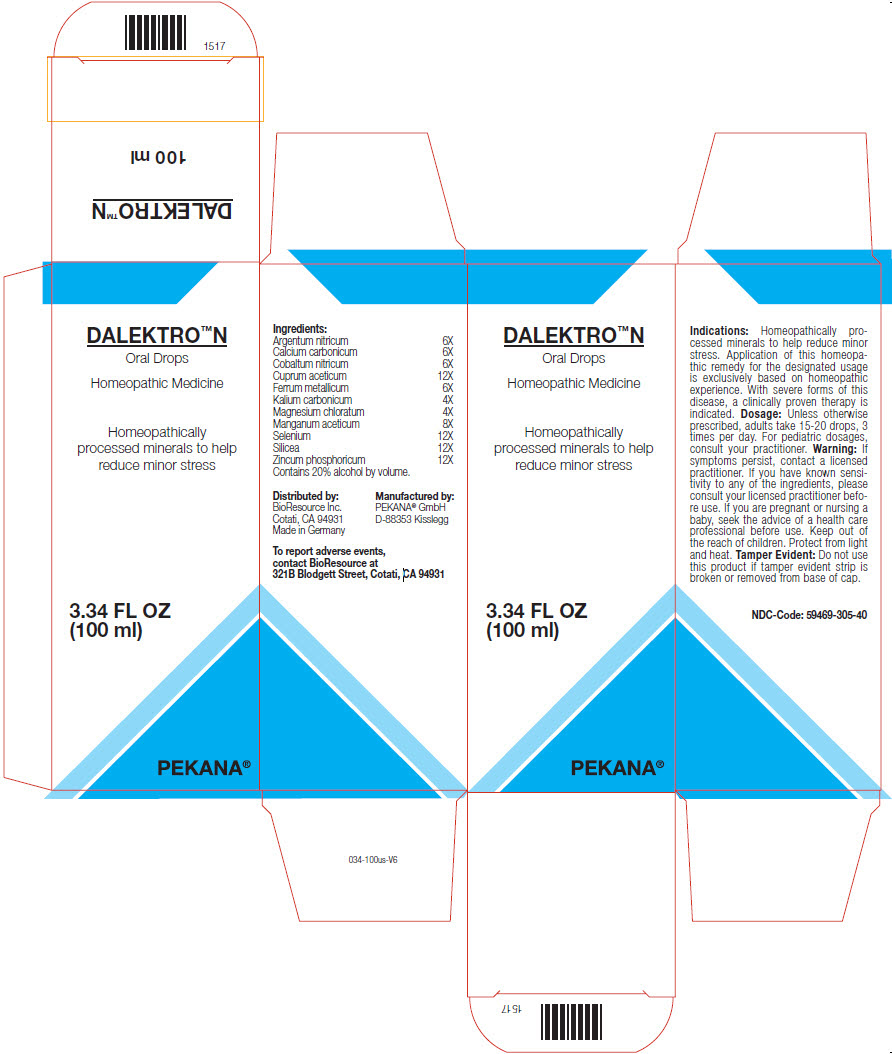 DRUG LABEL: DALEKTRO N
NDC: 59469-305 | Form: SOLUTION/ DROPS
Manufacturer: PEKANA Natruheilmittel GmbH
Category: homeopathic | Type: HUMAN OTC DRUG LABEL
Date: 20230111

ACTIVE INGREDIENTS: SILVER NITRATE 6 [hp_X]/100 mL; OYSTER SHELL CALCIUM CARBONATE, CRUDE 6 [hp_X]/100 mL; COBALTOUS NITRATE HEXAHYDRATE 6 [hp_X]/100 mL; CUPRIC ACETATE 12 [hp_X]/100 mL; IRON 6 [hp_X]/100 mL; POTASSIUM CARBONATE 4 [hp_X]/100 mL; MAGNESIUM CHLORIDE 4 [hp_X]/100 mL; MANGANESE ACETATE TETRAHYDRATE 8 [hp_X]/100 mL; SELENIUM 12 [hp_X]/100 mL; SILICON DIOXIDE 12 [hp_X]/100 mL; ZINC PHOSPHIDE 12 [hp_X]/100 mL
INACTIVE INGREDIENTS: WATER; ALCOHOL

DALEKTRO™ N

ACTIVE INGREDIENT

Ingredients:
Argentum nitricum | 6X
Calcium carbonicum | 6X
Cobaltum nitricum | 6X
Cuprum aceticum | 12X
Ferrum metallicum | 6X
Kalium carbonicum | 4X
Magnesium chloratum | 4X
Manganum aceticum | 8X
Selenium | 12X
Silicea | 12X
Zincum phosphoricum | 12X

INACTIVE INGREDIENT

Contains 20% alcohol by volume.

Indications

PURPOSE

Homeopathically processed minerals to help reduce minor stress. Application of this homeopathic remedy for the designated usage is exclusively based on homeopathic experience. With severe forms of this disease, a clinically proven therapy is indicated.

Dosage

Unless otherwise prescribed, adults take 15-20 drops, 3 times per day. For pediatric dosages, consult your practitioner.

Warning

If symptoms persist, contact a licensed practitioner. If you have known sensitivity to any of the ingredients, please consult your licensed practitioner before use. If you are pregnant or nursing a baby, seek the advice of a health care professional before use.

Keep out of the reach of children.

STORAGE AND HANDLING

Protect from light and heat.

Tamper Evident

Do not use this product if tamper evident strip is broken or removed from base of cap.

QUESTIONS

To report adverse events, contact BioResource at 321B Blodgett Street, Cotati, CA 94931

Distributed by:
BioResource Inc.
Cotati, CA 94931

Manufactured by:
PEKANA® GmbH
D-88353 Kisslegg

PRINCIPAL DISPLAY PANEL - 100 ml Bottle Box

DALEKTRO™N

Oral Drops

Homeopathic Medicine

Homeopathically
processed minerals to help
reduce minor stress

3.34 FL OZ
(100 ml)

PEKANA®